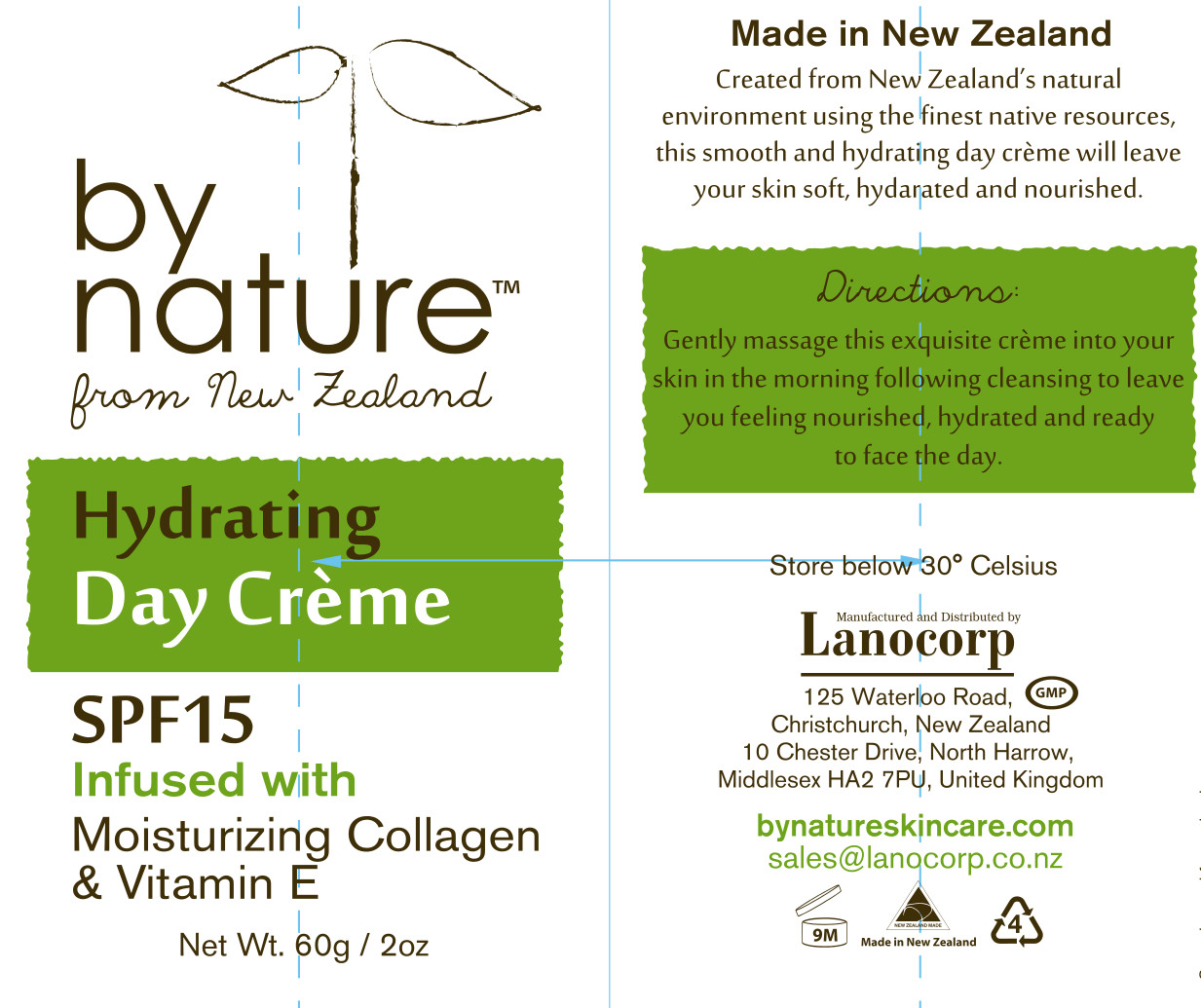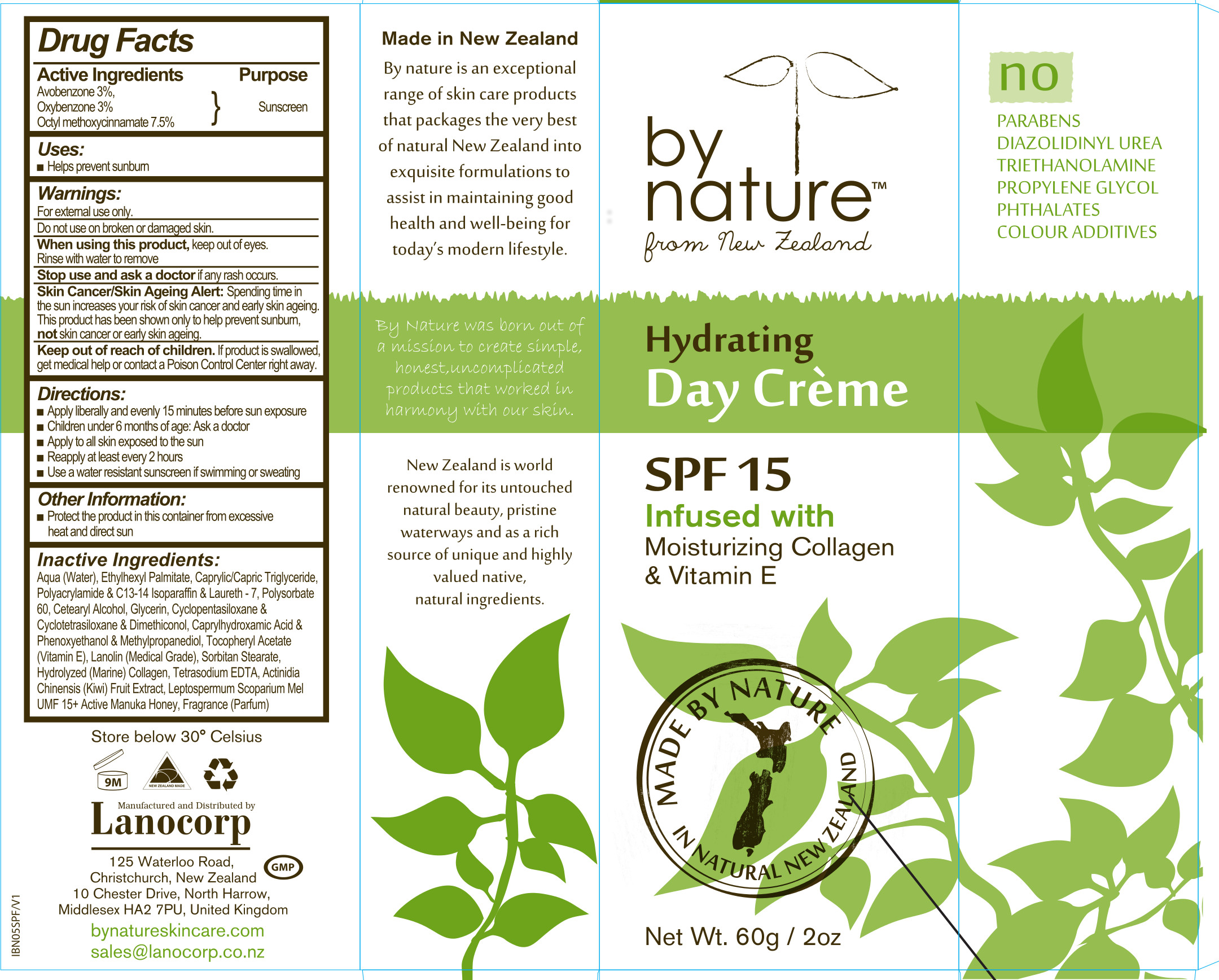 DRUG LABEL: By Nature Hydrating
NDC: 43617-3416 | Form: CREAM
Manufacturer: Lanocorp Pacific Ltd
Category: otc | Type: HUMAN OTC DRUG LABEL
Date: 20140812

ACTIVE INGREDIENTS: AVOBENZONE  1.5 g/50 g; OXYBENZONE 1.5 g/50 g; OCTINOXATE 7.5 g/50 g
INACTIVE INGREDIENTS: Water; Ethylhexyl palmitate; Tricaprylin; Tricaprin; SODIUM ACRYLOYLDIMETHYLTAURATE-ACRYLAMIDE COPOLYMER (1:1; 90000-150000 MPA.S); C13-14 Isoparaffin; Laureth-7; Polysorbate 60; Cetostearyl Alcohol; Glycerin; Cyclomethicone 5; Cyclomethicone 4; Dimethiconol (41 MPA.S); Caprylhydroxamic acid; Phenoxyethanol; Methylpropanediol; ALPHA-TOCOPHEROL ACETATE; Lanolin; Sorbitan monostearate; HYDROLYSED MARINE COLLAGEN (ENZYMATIC; 2000 MW); EDETATE SODIUM; KIWI FRUIT; HONEY

Drug Facts

ACTIVE INGREDIENTS
Avobenzone 3%
Oxybenzone 3%
Octylmethoxycinnamate 7.5%

USES
Helps prevent sunburn

WARNINGS
For external use only. Do not use on broken or damaged skin.
Skin Cancer/Skin Ageing Alert: Spending time in the sun increases your risk of skin cancer and early skin ageing. This product has been shown only to help prevent sunburn, not skin cancer or early skin ageing.

When using this product, keep out of eyes. Rinse with water to remove.

Stop use and ask a doctor if any rush occurs.

Keep out of reach of children.
Keep out of reach of children. If product is swalowed, get medical help or contact a Poison Control Center right away.

DIRECTIONS
Apply liberally and evenly 15 minutes before sun exposure
Children under 6 months of age: Ask a doctor
Apply to all skin exposed to the sun
Reapply at least every 2 hours
Use a water resistant sunscreen if swimming or sweating

ACTIVE INGREDIENTS
Avobenzone 3%
Oxybenzone 3%
Octyl methoxycinnamate 7.5%

PURPOSE

Sunscreen

INACTIVE INGREDIENTS
Water
Ethylhexyl palmitate
Caprylic triglyceride
Capric triglyceride
Polyacrylamide
c13-14 Isoparaffin
Laureth-7
Polysorbate 60
Cetearyl alcohol
Glycerin
Cyclopentasiloxane
Clyclotetrasiloxane
dimethiconol
Caprylhydroxamic acid
phenoxyethanol
methylpropanediol
tocopheryl acetate (vitamin e)
lanolin (medical grade)
Sorbitan stearate
Hydrolyzed (Marine) collagen
Tetrasodium EDTA
Actinidia chinensis (kiwi) fruit extract
Leptospermum scoparium Mel UMF 15+ Active Manuka Honey